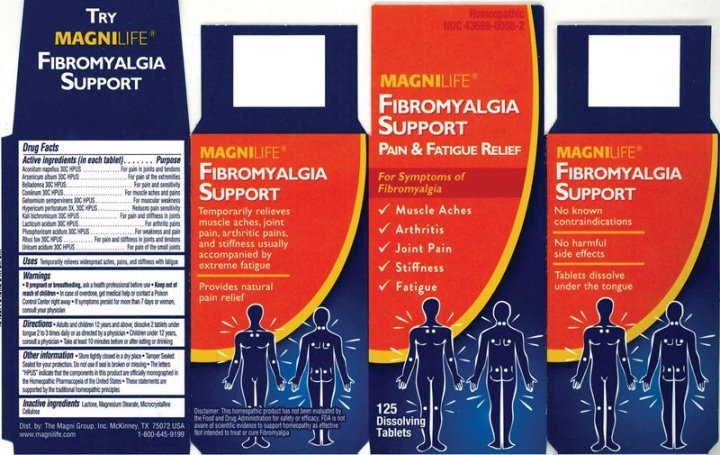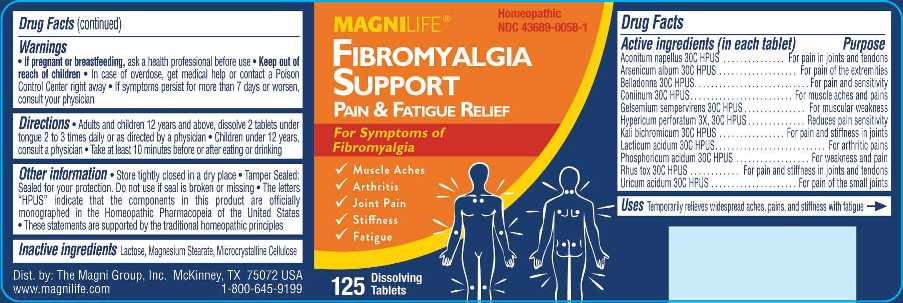 DRUG LABEL: Fibromyalgia Support
NDC: 43689-0058 | Form: TABLET
Manufacturer: The Magni Company
Category: homeopathic | Type: HUMAN OTC DRUG LABEL
Date: 20251009

ACTIVE INGREDIENTS: ACONITUM NAPELLUS WHOLE 30 [hp_C]/1 1; ARSENIC TRIOXIDE 30 [hp_C]/1 1; ATROPA BELLADONNA 30 [hp_C]/1 1; CONIINE 30 [hp_C]/1 1; GELSEMIUM SEMPERVIRENS ROOT 30 [hp_C]/1 1; HYPERICUM PERFORATUM WHOLE 3 [hp_X]/1 1; POTASSIUM DICHROMATE 30 [hp_C]/1 1; LACTIC ACID, DL- 30 [hp_C]/1 1; PHOSPHORIC ACID 30 [hp_C]/1 1; TOXICODENDRON PUBESCENS LEAF 30 [hp_C]/1 1; URIC ACID 30 [hp_C]/1 1
INACTIVE INGREDIENTS: LACTOSE MONOHYDRATE; MAGNESIUM STEARATE; CELLULOSE, MICROCRYSTALLINE

DRUG FACTS:

ACTIVE INGREDIENTS:

Aconitum Napellus 30C, Arsenicum Album 30C, Belladonna 30C, Coniinum 30C, Gelsemium Sempervirens 30C, Hypericum Perforatum 3X, 30C, Kali Bichromicum 30C, Lacticum Acidum 30C, Phosphoricum Acidum 30C, Rhus Tox 30C, Uricum Acidum 30C.

PURPOSE:

Aconitum Napellus – For pain in joints and tendons, Arsenicum Album – For pain of the extremities, Belladonna – For pain and sensitivity, Coniinum – For muscle aches and pains, Gelsemium Sempervirens – For muscular weakness, Hypericum Perforatum – Reduces pain sensitivity, Kali Bichromicum – For pain and stiffness in joints, Lacticum Acidum – For arthritic pains, Phosphoricum Acidum – For weakness and pain, Rhus Tox – For pain and stiffness in joints and tendons, Uricum Acidum – For pain of the small joints

USES:

Temporarily relieves widespread aches, pains, and stiffness with fatigue

WARNINGS:

• If pregnant or breastfeeding, ask a health professional before use

• Keep out of reach of children In case of overdose, get medical help or contact a Poison Control Center right away

• If symptoms persist for more than 7 days or worsen, consult your physician

Keep out of reach of children. In case of overdose, get medical help or contact a Poison Control Center right away

DIRECTIONS:

• Adults and children 12 years and above, dissolve 2 tablets under tongue 2 to 3 times daily or as directed by a physician

• Children under 12 years, consult a physician

• Take at least 10 minutes before or after eating or drinking

OTHER INFORMATION:

• Store tightly closed in a cool, dry place

• Tamper Sealed: Sealed for your protection. Do not use if seal is broken or missing

• The letters "HPUS" indicate that the components in this product are officially monographed in the Homeopathic Pharmacopeia of the United

States

• These statements are supported by the traditional homeopathic principles

INACTIVE INGREDIENTS:

Lactose, Magnesium Stearate, Microcrystalline Cellulose

QUESTIONS:

Dist. by: The Magni Group, Inc. McKinney, TX 75072 USA

www.magilife.com 1-800-645-9199

PACKAGE LABEL DISPLAY:

MAGNILIFE Homeopathic
FIBROMYALGIA NDC 43689-0058-1
SUPPORT

PAIN & FATIGUE RELIEF

For symptoms of

Fibromyalgia

√ Muscle Aches
√ Arthritis
√ Joint Pain
√ Stiffness
√ Fatigue

125 Dissolving

Tablets